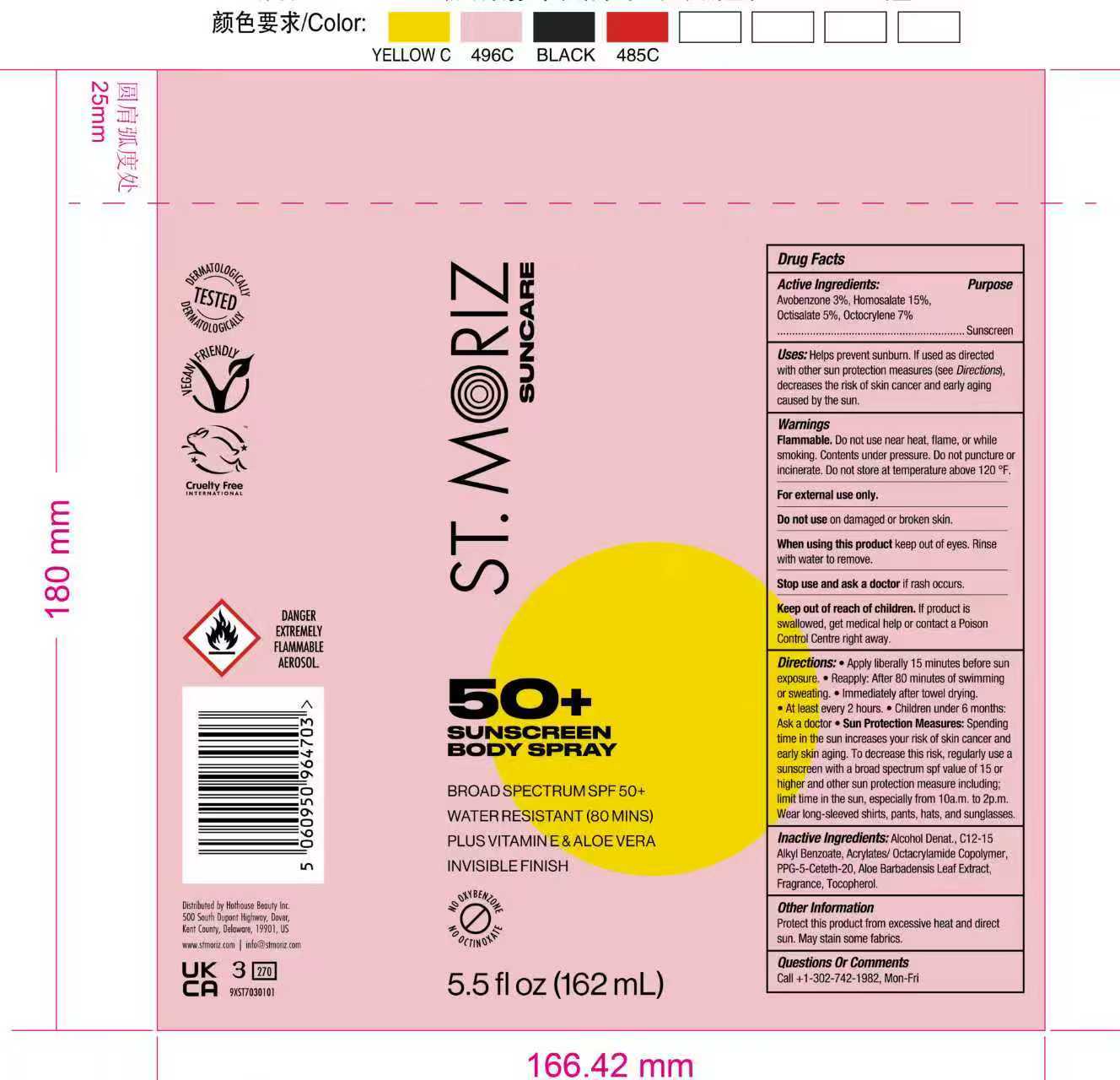 DRUG LABEL: St Moriz Suncare SPF 50 Sunscreen Body
NDC: 82723-020 | Form: SPRAY
Manufacturer: Aopline Health Industry Technology (Guangzhou) Co., Ltd.
Category: otc | Type: HUMAN OTC DRUG LABEL
Date: 20251202

ACTIVE INGREDIENTS: ETHYLHEXYL SALICYLATE 5 g/100 mL; BUTYL METHOXYDIBENZOYLMETHANE 3 g/100 mL; OCTOCRYLENE 7 g/100 mL; HOMOSALATE 15 g/100 mL
INACTIVE INGREDIENTS: PPG-5-CETETH-20; ALCOHOL; FRAGRANCE 13576; C12-15 ALKYL BENZOATE; TOCOPHEROL; ALOE VERA LEAF

ACTIVE INGREDIENT

Homosalate
Octocrylene
Ethylhexyl Salicylate
(Octisalate)
Butyl Methoxydibenzoylmethane
(Avobenzone)

PURPOSE

Helps prevent sunburn. lf used as directedwith other sun protection measures (see Directions).decreases the risk of skin cancer and early agingcaused by the sun.

Keep out of reach of children. if product isswallowed, get medical help or contact a PoisonControl Centre right away

WARNINGS

WarningsFlammable. Do nat use near heat, flame, or whilesmoking. Contents under pressure. Do not puncture orincinerate, Do not store at temperature above 120 °F
For external use only.

INACTIVE INGREDIENT

Inactive Ingredients: Alcohol Denat. C12-15Alkyl Benzoate, Acrylates/ 0ctacrylamide Copolymer,PPG-5-Ceteth-20, Aloe Barbadensis Leaf ExtractFragrance, Tocopherol.

INDICATIONS AND USAGE

Sun Protection Measures: Spendingtime in the sun increases your risk of skin cancer andearly skin aging. To decrease this risk, regularly use asunscreen with a broad spectrum spf value of 15 orhigher and other sun protection measure including:limit time in the sun, especially from 10a.m. to 2p.m.Wear long-sleeved shirts, pants, hats, and sunglasses

DOSAGE AND ADMINISTRATION

Apply liberally 15 minutes before sunexposure, Reapply: After 80 minutes of swimmingor sweating." immediately after towel dryingAt least every 2 hours. Children under 6 months.Ask a doctor